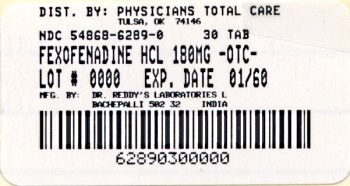 DRUG LABEL: Fexofenadine hydrochloride
NDC: 54868-6289 | Form: TABLET
Manufacturer: Physicians Total Care, Inc.
Category: otc | Type: HUMAN OTC DRUG LABEL
Date: 20110425

ACTIVE INGREDIENTS: Fexofenadine Hydrochloride 180 mg/1 1
INACTIVE INGREDIENTS: SILICON DIOXIDE; CROSCARMELLOSE SODIUM; magnesium stearate; mannitol; POWDERED CELLULOSE; FD&C RED NO. 40; HYPROMELLOSE 2910 (6 MPA.S); FERRIC OXIDE BLACK; polyethylene glycol 400; TITANIUM DIOXIDE; STARCH, CORN

Fexofenadine HCl Tablets USP

Active ingredient(s)

Fexofenadine HCl USP, 180 mg

Purpose

Antihistamine

Use(s)

temporarily relieves these symptoms due to hay fever or otherupper respiratory allergies:

- runny nose
- itchy, watery eys
- sneezing
- itching of the nose or Throad

Warnings

Do not use

if you have ever had an allergic reaction to this product or any of its ingredients.

Ask a doctor before use if

you have kidney disease. Your doctorshould determine if you need a different dose.

When using this product

do not take more than directed

- do not take at the same time as aluminum or magnesium antacids
- do not take with fruit juices (see Directions)

Stop use and ask doctor if

Allergy

an allergic reaction to this product occurs. Seek medical help right away.

Pregnancy/Breastfeeding

ask a health professional before use.

Keep out of reach of children

In case of overdose, get medical help or contact a Poison Control Center right away.

Directions

adults and children 12 years of age and over | take one 180 mg tablet with water once a day; do not take more than 1 tablet in 24 hours
children under 12 years of age | do not use
Adults 65 years of age and older | ask a doctor
consumers with kidney disease | ask a doctor

Other information

safety sealed: do not use if carton is opened or if individual blister units are torn or opened.

Storage

store between 20° - 25°C (68° - 77°F)

protect from excessive moisture

Inactive ingredients

colloidal silicon dioxide, corn starch, croscarmellose sodium, magnesium stearate, mannitol, and powdered cellulose, opadry pink 03B54504 containing FD&C Red no. 40, hypromellose, iron oxide black, polyethylene glycol and titanium dioxide.

Questions

call toll-free 1-888-375-3784

Manufactured by:

Dr. Reddy’s Laboratories Louisiana LLC,

8800 Line Ave Shreveport, LA, 71106.

OR

Manufactured by:

Dr. Reddy’s Laboratories Limited

Bachepalli - 502 325 INDIA

Additional barcode labeling by:
Physicians Total Care, Inc.
Tulsa, OK 74146

Principal Display Panel

Fexofenadine HCl USP, 180 mg

NDC 54868-6289-0